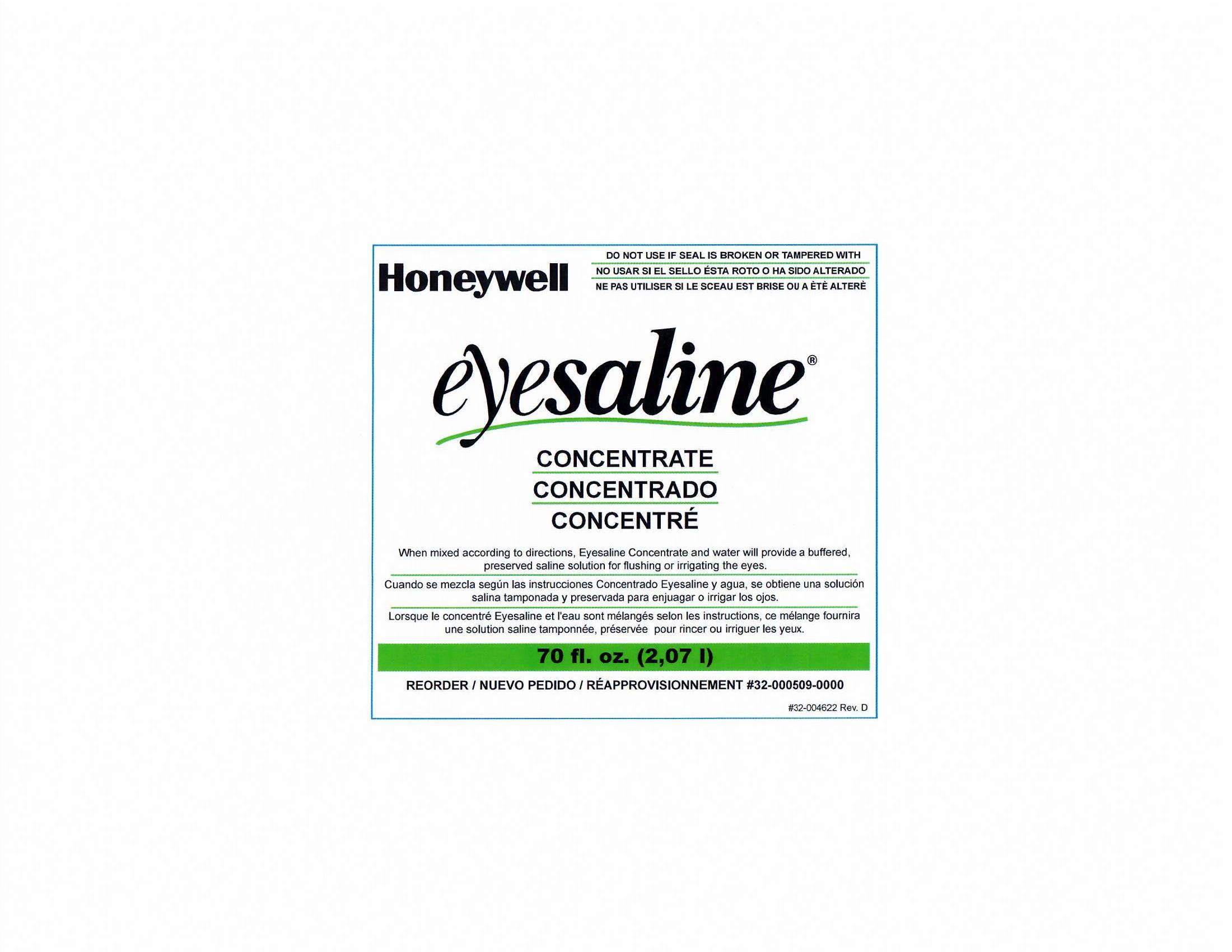 DRUG LABEL: Eyesaline  Concentrate
NDC: 64809-104 | Form: LIQUID
Manufacturer: Sperian Eye & Face Protection Inc.
Category: otc | Type: HUMAN OTC DRUG LABEL
Date: 20180321

ACTIVE INGREDIENTS: WATER 92.2 mL/100 mL
INACTIVE INGREDIENTS: SODIUM PHOSPHATE, MONOBASIC, MONOHYDRATE; SODIUM PHOSPHATE, DIBASIC, ANHYDROUS; SODIUM CHLORIDE; EDETATE DISODIUM; BENZALKONIUM CHLORIDE

Sperian Eyesaline Concentrate

Active Ingredient

Purified water 93%

Purpose

Eyewash

Uses

- For flushing or irrigating the eye to remove loose foreign material, air pollutants, or chlorinated water.

Warnings

For external use only- Obtain immidiate medical treatment for all open wounds in or near the eyes. To avoid contamination, do not touch tip of container to any surface. Replace cap after use.

Do not use

- in concentrated form
- while wearing contact lenses
- if solution changes color or becomes cloudy
- for injection
- in intraocular surgery
- internally
- if eye is lacerated or object is embedded
- if seal is broken

Stop use and consult a doctor if you have

- changes in vision
- continued reddness, irritation or pain, or if the condition worsens or persists

Keep out of reach of children

If swallowed, get medical help or contact a Poison Control Center right away.

Directions

- Concentrate must be diluted (1) part concentrate to (10) parts potable water before use
- Prepare sufficient quantity of constituted eyewash solution in advance of an emergency
- Mix concentrate with potable water to prepare eyewash solution as follows:
- Determine quantity of eyewash solution required
- Follow sanitary procedures
- Wear protective eyewear and gloves
- Pour 1/3 of required amount of potable water into mixing container or eyewash unit
- Add 1/3 of required amount of concentrate to water
- Agitate or mix thoroughly
- Repeat until required amount of solution is prepared
- Properly dispose of empty bottle after use

Do not reuse.

- Replace solution no longer than (6) months after mixing

Other information

Do not freeze

Inactive ingredients

benzalkonium chloride, edetate disodium, sodium chloride, sodium phosphate dibasic, sodium phosphate monobasic

Questions?

Call 1-800-430-5490

Sperian Eye and Face Protection Inc
(a Honeywell Company)
825 East Highway 151
Platteville, WI 53818 USA